DRUG LABEL: ANTIBACTERIAL Hand Sanitizer
NDC: 74534-011 | Form: LIQUID
Manufacturer: Guangzhou Dedo Pharmaceutical Co.,Ltd
Category: otc | Type: HUMAN OTC DRUG LABEL
Date: 20200423

ACTIVE INGREDIENTS: ALCOHOL 24 g/100 g; CHLOROXYLENOL 0.13 g/100 g
INACTIVE INGREDIENTS: CARBOMER HOMOPOLYMER, UNSPECIFIED TYPE; POLYOXYL 40 HYDROGENATED CASTOR OIL; WATER; TROLAMINE; DMDM HYDANTOIN

Active Ingredient(s)

Parachlormetaxylenol-0.13%.Ethanol 24%.

Purpose

Antimicrobial

Use

it is suitable for dally bacteriostasis of hand,Bacleriostasis,sterillzation.wash-free.Contain antibacterial components, effectively inhibit staphylococcus aureus and escherichia.coli;

Warnings

for external use only.

do not use in or near the eyes.In case of contact.rinse eyes thoroughly with water.Stop use and ask doctor if irritation or rash appears and lasts.

Keep out of teach for children.

If swallowed,get medical help or contact a Poison Control Center right away.

Directions

Place enough Product in your palm to thoroughly spread on both hands and rub into the skin until dry.

Children under 6 years of age should be supervised when using this product.

Other information

Please keep it in a cool and ventilated place.

Inactive ingredients

Water(Aqua).Carbomer.Triethanolamine,DMDM hydantoin,PEG-40 hydrogenated castor oil, Essence.